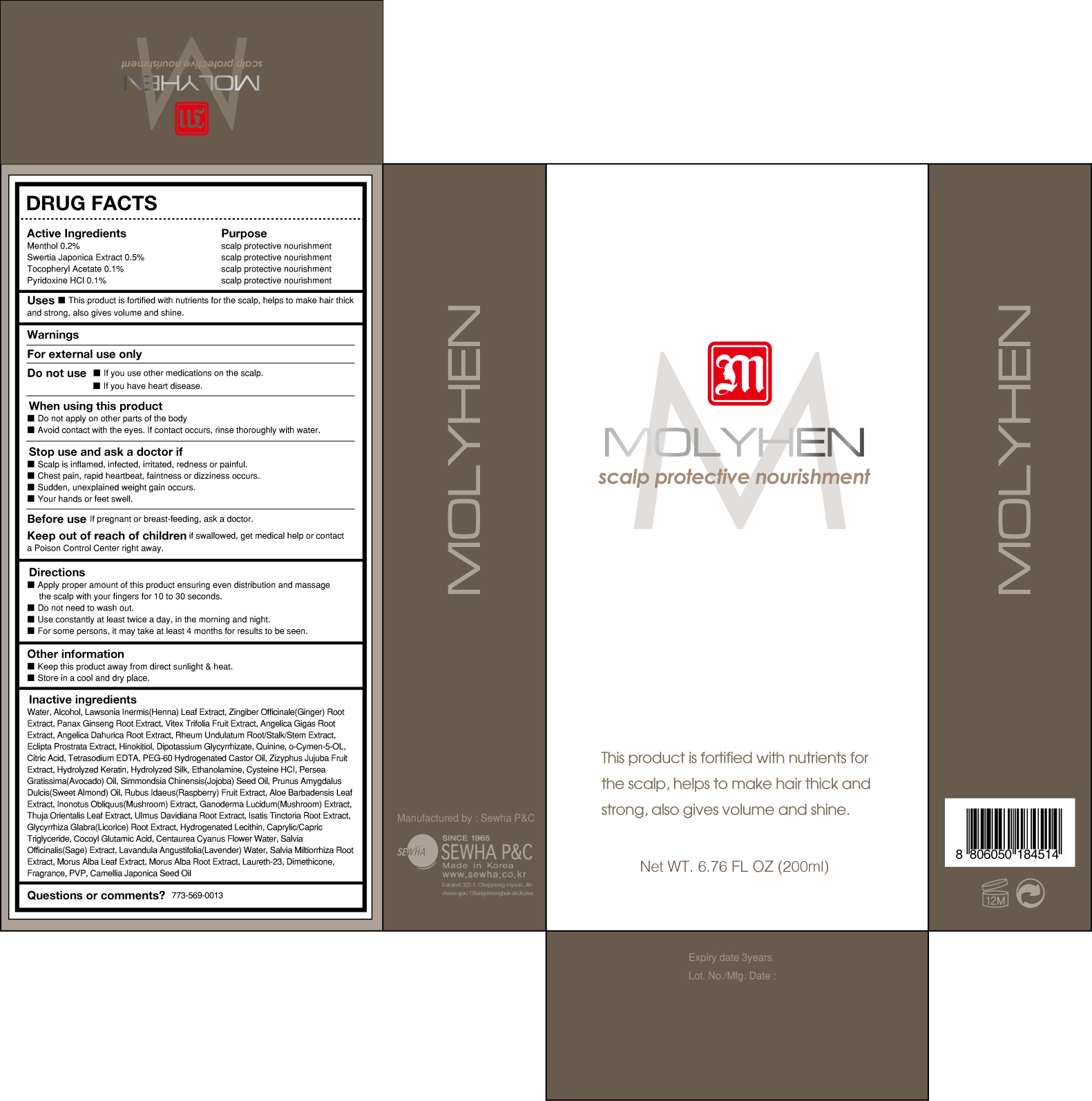 DRUG LABEL: MOLYHEN
NDC: 50629-1010 | Form: LIQUID
Manufacturer: SEWHA P&C INC
Category: otc | Type: HUMAN OTC DRUG LABEL
Date: 20120517

ACTIVE INGREDIENTS: MENTHOL 4 mL/200 mL; .ALPHA.-TOCOPHEROL ACETATE, D- 2 mL/200 mL; SWERTIA JAPONICA 10 mL/200 mL; PYRIDOXINE HYDROCHLORIDE 2 mL/200 mL
INACTIVE INGREDIENTS: WATER; ALCOHOL; LAWSONIA INERMIS LEAF; ZINGIBER CASSUMUNAR ROOT; ASIAN GINSENG; VITEX TRIFOLIA FRUIT; ANGELICA GIGAS ROOT; ANGELICA DAHURICA ROOT; ECLIPTA PROSTRATA LEAF; .BETA.-THUJAPLICIN; GLYCYRRHIZINATE DIPOTASSIUM; QUININE; O-CYMEN-5-OL; CITRIC ACID MONOHYDRATE; EDETATE SODIUM; POLYOXYL 60 HYDROGENATED CASTOR OIL ; JUJUBE FRUIT; MONOETHANOLAMINE; CYSTEINE HYDROCHLORIDE; AVOCADO OIL; JOJOBA OIL; ALMOND OIL; RASPBERRY; ALOE VERA LEAF; INONOTUS OBLIQUUS FRUITING BODY; REISHI; PLATYCLADUS ORIENTALIS LEAF; ULMUS DAVIDIANA ROOT; ISATIS TINCTORIA ROOT; GLYCYRRHIZA GLABRA; HYDROGENATED SOYBEAN LECITHIN; MEDIUM-CHAIN TRIGLYCERIDES; SODIUM COCOYL GLUTAMATE; CENTAUREA CYANUS FLOWER; SAGE; LAVENDER OIL; SALVIA MILTIORRHIZA ROOT; MORUS ALBA LEAF; MORUS ALBA ROOT; LAURETH-23; DIMETHICONE ; CROSPOVIDONE; CAMELLIA JAPONICA SEED OIL

MOLYHEN

Drug Facts

Active Ingredients :
Menthol 0.2%
Swertia japonica extract 0.5%
Tocopheryl acetate 0.1%
Pyridoxine HCl 0.1%

Purpose

scalp protective nourishment

Keep out of reach of children if swallowed, get medical help or contact a Poison Control Center right away.

Indication & Usage

Directions
■ Apply proper amount of this product ensuring even distribution and massage the scalp with
your fingers for 10 to 30 seconds.
■ Do not need to wash out.
■ Use constantly at least twice a day, in the morning and night.
■ For some persons, it may take at least 4 months for results to be seen.

Warnings

Warning

For external use only

Do not use
■ If you use other medications on the scalp.
■ If you have heart disease.

When using this product
■ Do not apply on other parts of the body
■ Avoid contact with the eyes. In case of accidental contact, rinse eyes with large amounts of cool
tap water
■ If pregnant or breast-feeding, ask a health care professional before use.

Dosage & Administration

Uses
■ This product is fortified with nutrients for the scalp, helps to make hair thick and strong, also gives volume and shine.

Inactive Ingredient

Water, Alcohol, Lawsonia Inermis Extract, Zingiber Officinale(Ginger) Root Extract, Panax Ginseng Root Extract, Vitex Trifolia Fruit Extract, Angelica Gigas Root Extract, Angelica Dahurica Root Extract, Rheum Undulatum Root/Stalk/Stem Extract, Eclipta Prostrata Extract, Hinokitiol, Dipotassium Glycyrrhizate, Quinine, O-Cymen-5-Ol, Citric Acid, Tetrasodium EDTA, PEG-60 Hydrogenated Castor Oil, Zizyphus Jujuba Fruit Extract, Hydrolyzed Keratin, Hydrolyzed Silk, Ethanolamine, Cysteine HCI, Persea Gratissima(Avocado) Oil, Simmondsia Chinensis(Jojoba) Seed Oil, Prunus Amygdalus Dulcis(Sweet Almond) Oil, Rubus Idaeus(Raspberry) Fruit Extract, Aloe Barbadensis Leaf Extract, Inonotus Obliquus(Mushroom) Extract, Ganoderma Lucidum(Mushroom) Extract, Thuja Orientalis Leaf Extract, Ulmus Davidiana Root Extract, Isatis Tinctoria Root Extract, Glycyrrhiza Glabra(Licorice) Root Extract, Hydrogenated Lecithin, Caprylic/Capric Triglyceride, Cocoyl Glutamic Acid, Centaurea Cyanus Flower Water, Salvia Officinalis(Sage) Extract, Lavandula Angustifolia(Lavender) Water, Salvia Miltiorrhiza Root Extract, Morus Alba Leaf Extract, Morus Alba Root Extract, Laureth-23, Dimethicone, Fragrance, PVP, Camellia Japonica Seed Oil

MOLYHEN

200ml/ 6.76 fl.oz